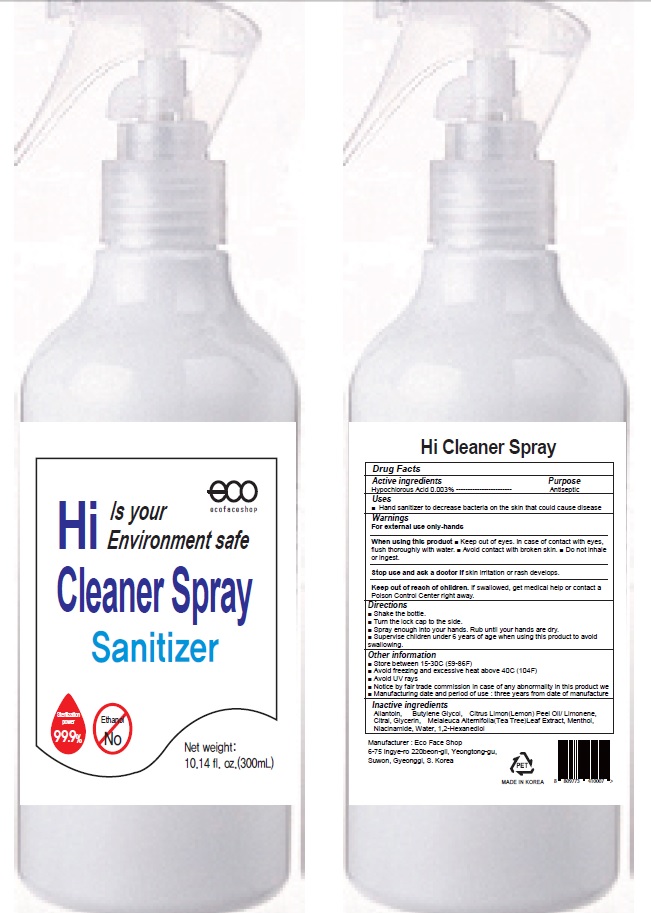 DRUG LABEL: Hi Cleaner
NDC: 71672-040 | Form: SPRAY
Manufacturer: Eco Face Shop
Category: otc | Type: HUMAN OTC DRUG LABEL
Date: 20201015

ACTIVE INGREDIENTS: HYPOCHLOROUS ACID 0.009 g/300 mL
INACTIVE INGREDIENTS: Allantoin; Butylene Glycol; LEMON OIL; LIMONENE, (+)-; CITRAL; MELALEUCA ALTERNIFOLIA LEAF; Glycerin; Menthol; Niacinamide; Water; 1,2-Hexanediol

ACTIVE INGREDIENT

Hypochlorous Acid 0.003%

INACTIVE INGREDIENTS

Allantoin, Butylene Glycol, Citrus Limon (Lemon) Peel Oil/ Limonene, Citral, Glycerin, Melaleuca Alternifolia(Tea Tree)Leaf Extract, Menthol, Niacinamide, Water, 1,2-Hexanediol

PURPOSE

Antiseptic

WARNINGS

For external use only-hands.
--------------------------------------------------------------------------------------------------------
When using this product ■ Keep out of eyes. In case of contact with eyes, flush thoroughly with water. ■ Avoid contact with broken skin. ■ Do not inhale or ingest.

--------------------------------------------------------------------------------------------------------

Stop use and ask a doctor if skin irritation or rash develops.

Keep out of reach of children. If swallowed, get medical help or contact a Poison Control Center right away.

Uses

■ Hand sanitizer to decrease bacteria on the skin that could cause disease

Directions

■ Shake the bottle.
■ Turn the lock cap to the side.
■ Spray enough into your hands. Rub until your hands are dry.
■ Supervise children under 6 years of age when using this product to avoid swallowing.

Other information

■ Store between 15-30C (59-86F)
■ Avoid freezing and excessive heat above 40C (104F)
■ Avoid UV rays
■ Notice by fair trade commission in case of any abnormality in this product we ■ Manufacturing date and period of use : three years from date of manufacture